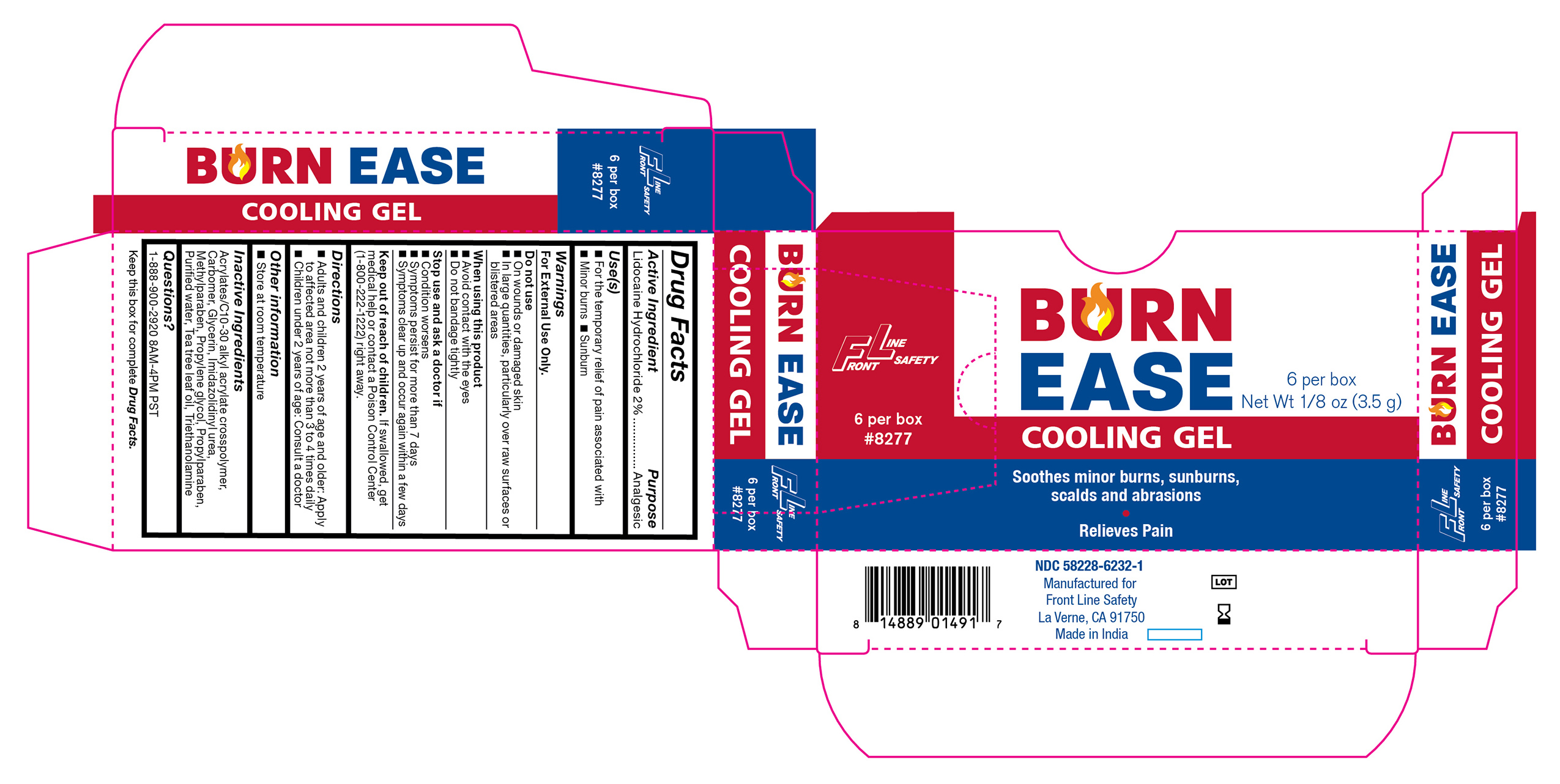 DRUG LABEL: Burn Ease 3.5g
NDC: 58228-6232 | Form: GEL
Manufacturer: Front Line Safety
Category: otc | Type: HUMAN OTC DRUG LABEL
Date: 20251215

ACTIVE INGREDIENTS: LIDOCAINE HYDROCHLORIDE 2 g/100 g
INACTIVE INGREDIENTS: GLYCERIN; METHYLPARABEN; WATER; PROPYLENE GLYCOL; CARBOMER COPOLYMER TYPE B (ALLYL PENTAERYTHRITOL CROSSLINKED); PROPYLPARABEN; IMIDUREA; TEA TREE OIL; TROLAMINE; CARBOMER HOMOPOLYMER, UNSPECIFIED TYPE

FL-3832

Active Ingredient

Lodocaine Hydrochloride 2%

Purpose

Analgesic

Use(s)

• For the temporary relief of pain associated with • Minor burns • Sunburn

Warnings

For External Use Only

Do not use

• On wounds or damaged skin

• Large quanities, particularly over raw surfaces or blistered areas

When using this product

• Avoid contact with the eyes

• Do not bandage tightly

Stop use and ask a doctor if

• Condition worsens

• Symptoms persist for more than 7 days

• Symptoms clear up and occur again within a few days

Keep out of reach of children

If swallowed, get medical help or contact a Poison Control Center (1-800-222-1222) right away.

Directions

• Adults and children 2 years of age and older: Apply to affected area not more than 3 to 4 times daily

• Children under 2 year of age: Consult a doctor

Other information

• Store at room temperature

Inactive Ingredients

Acrylates/C10-30 Alkyl Acrylate Crosspolymer, Carbomer, Glycerin, Imidazolidinyl Urea, Methylparaben, Propylene Glycol, Propylparaben, Purified Water, Tea Tree Leaf Oil, Triethanolamine

Questions?

1-888-900-2920 8AM-4PM PST

Label

FL-3832